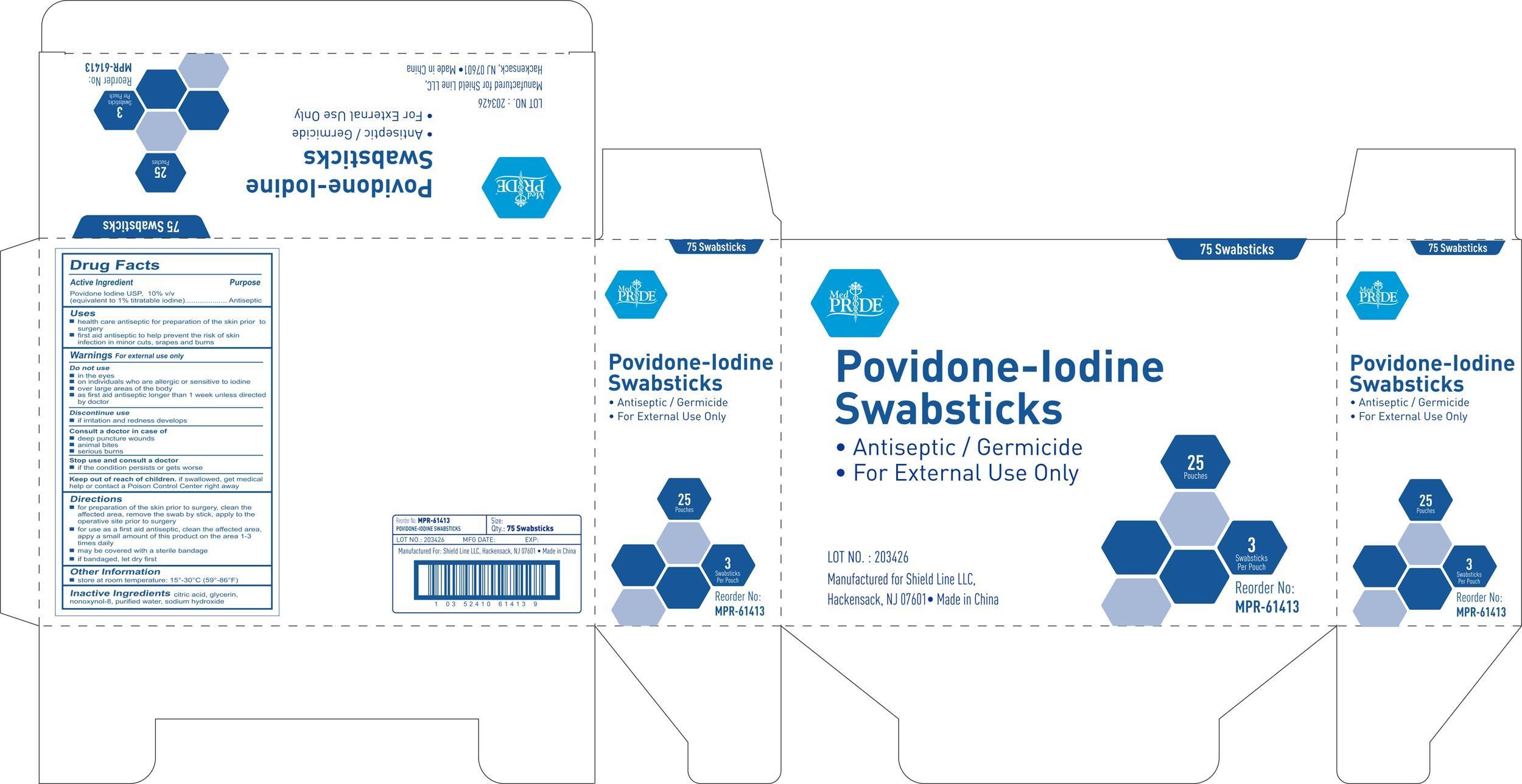 DRUG LABEL: MedPride
NDC: 52410-6141 | Form: SOLUTION
Manufacturer: Shield Line LLC
Category: otc | Type: HUMAN OTC DRUG LABEL
Date: 20191118

ACTIVE INGREDIENTS: POVIDONE-IODINE 0.1 g/1 1
INACTIVE INGREDIENTS: CITRIC ACID MONOHYDRATE; GLYCERIN; NONOXYNOL-8; WATER; SODIUM HYDROXIDE

Drug Facts

Active Ingredient

Povidone Iodine 10% v/v

(equivalent to 1% titratable iodine)

Purpose

Antiseptic

Uses

■ health care antiseptic for preparation of the skin prior to surgery

■ first aid antiseptic to help prevent the risk of skin infection in minor cuts, scrapes and burns

Warnings

For external use only

Do not use

■ in the eyes

■ on individuals who are allergic or sensitive to iodine

■ over large areas of the body

■ as first aid antiseptic longer than 1 week unless directed by doctor

Discontinue use

■ if irritation and redness develops

Consult a doctor in case of

■ deep puncture wounds

■ animal bites

■ serious burns

Stop use and ask a doctor if

■ if the condition persist or gets worse

Keep out of reach of children

If swallowed contact a doctor or Poison Control Center right away.

Directions

■ for preparation of the skin prior to surgery, clean the affected area, remove the swab by stick, apply to the operative site prior to surgery

■ for use as a first aid antiseptic, clean the affected area, apply a small amount of this product on the area 1-3 times daily

Other Information

■ store at room temperature:15-30C (59-86F)

Inactive Ingredients

citric acid, glycerin, nonoxynol-8, purified water, sodium hydroxide